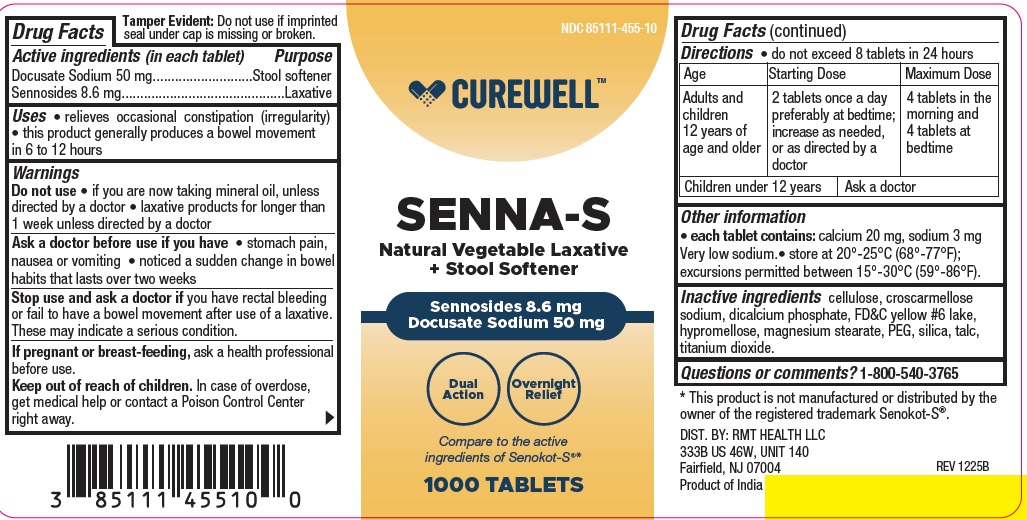 DRUG LABEL: Senna-S
NDC: 85111-455 | Form: TABLET
Manufacturer: RMT HEALTH LLC
Category: otc | Type: HUMAN OTC DRUG LABEL
Date: 20251231

ACTIVE INGREDIENTS: SENNOSIDES 8.6 mg/1 1; DOCUSATE SODIUM 50 mg/1 1
INACTIVE INGREDIENTS: CELLULOSE, MICROCRYSTALLINE; CROSCARMELLOSE SODIUM; CALCIUM PHOSPHATE, DIBASIC, ANHYDROUS; MAGNESIUM STEARATE; POLYETHYLENE GLYCOL, UNSPECIFIED; HYPROMELLOSES; FD&C YELLOW NO. 6; TITANIUM DIOXIDE; TALC; SILICON DIOXIDE

CRW 455b

Active ingredient (in each tablet)

Docusate Sodium 50 mg
Sennosides 8.6 mg

Purpose

Stool softener

Laxative

Uses

- relieves occasional constipation (irregularity)

- this product generally produces a bowel movement in 6 to 12 hours

Warnings

Do not use • if you are now taking mineral oil, unless
directed by a doctor • laxative products for longer than
1 week unless directed by a doctor
Ask a doctor before useif you have • stomach pain,
nausea or vomiting • noticed a sudden change in bowel
habits that lasts over two weeks
Stop use and ask a doctor if you have rectal bleeding
or fail to have a bowel movement after use of a laxative.
These may indicate a serious condition.
If pregnant or breast-feeding, ask a health professional
before use.

Keep out of reach of children. In case of overdose, get medical help or contact a Poison Control Center right away.

Directions

• do not exceed 8 tablets in 24 hours

Age | Starting Dose | Maximum Dose
adults and children 12 years of age and older | 2 tablets once a day preferably at bedtime; increase as needed, or as directed by a doctor | 4 tablets in the morning and 4 tablets at bedtime
children under 12 years | ask a doctor

Other information

- each tablet contains: calcium 20 mg, sodium 3 mg Very low sodium.
- store at 20°-25°C (68°-77°F); excursions permitted between 15°-30°C (59°-86°F).

Inactive ingredients

cellulose, croscarmellose sodium, dicalcium phosphate, FD&C yellow #6 lake, hypromellose, magnesium stearate, PEG, silica, talc, titanium dioxide.

Questions or comments?

1-800-540-3765